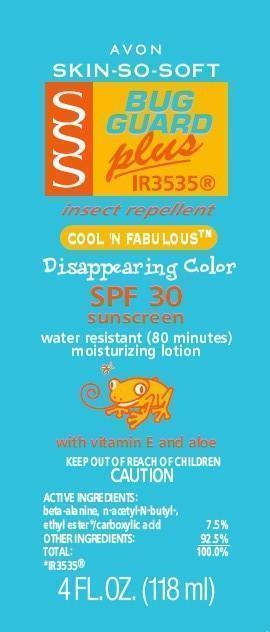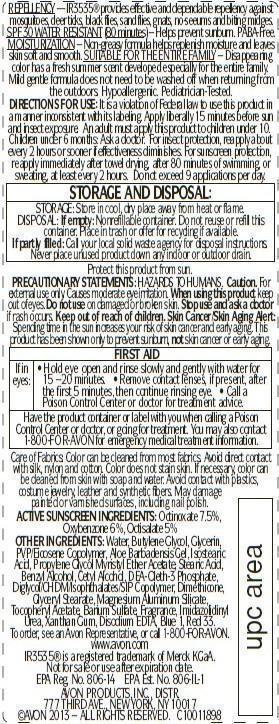 DRUG LABEL: Skin So Soft Bug Guard Plus IR3535
NDC: 10096-0071 | Form: LOTION
Manufacturer: New Avon LLC
Category: otc | Type: HUMAN OTC DRUG LABEL
Date: 20190101

ACTIVE INGREDIENTS: OCTINOXATE 75 mg/1 mL; OXYBENZONE 60 mg/1 mL; OCTISALATE 50 mg/1 mL
INACTIVE INGREDIENTS: WATER

SSS BG+ Cool N Fabulous Disappearing Color

INDICATIONS AND USAGE

Helps prevent sunburn

DOSAGE AND ADMINISTRATION

DIRECTIONS FOR USE: It is a violation of Federal law to use this product in a manner inconsistent with its labeling. Apply liberally 15 minutes before sun and insect exposure. An adult must apply this product to children under 10. Children under 6 months: Ask a doctor. For insect protection, reapply about every 2 hours or sooner if effectiveness diminishes. For sunscreen protection, reapply immediately after towel drying, after 80 minutes of swimming, or sweating, at least every 2 hours. Do not exceed 9 applications per day.

STORAGE AND HANDLING

STORAGE: Store in cool, dry place away from heat or flame.

Protect this product from sun.

WARNINGS

Caution. For external use only. Causes moderate eye irritation. When using this product keep out of eyes. Do not use on damaged or broken skin. Stop use and ask a doctor if rash occurs. Keep out of reach of children. Skin Cancer/Skin Aging Alert: Spending time in the sun increases your risk of skin cancer and early aging. This product has been shown only to prevent sunburn, not skin cancer or early aging.

ACTIVE INGREDIENT

ACTIVE SUNSCREEN INGREDIENTS: Octinoxate 7.5%, Oxybenzone 6%, Octisalate 5%

PURPOSE

sunscreen

INACTIVE INGREDIENT

OTHER INGREDIENTS: Water, Butylene Glycol, Glycerin, PVP/Eicosene Copolymer, Aloe Barbadensis Gel, Isostearic Acid, Propylene Glycol Myristyl Ether Acetate, Stearic Acid, Benzyl Alcohol, Cetyl Alcohol, DEA-Oleth-3 Phosphate, Diglycol/CHDM/Isophthalates/SIP Copolymer, Dimethicone, Glyceryl Stearate, Magnesium Aluminum Silicate, Tocopheryl Acetate, Barium Sulfate, Fragrance, Imidazolidinyl Urea, Xanthan Gum, Disodium EDTA, Blue 1, Red 33.